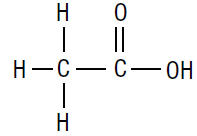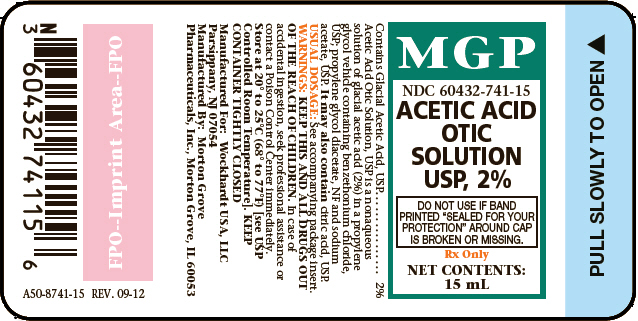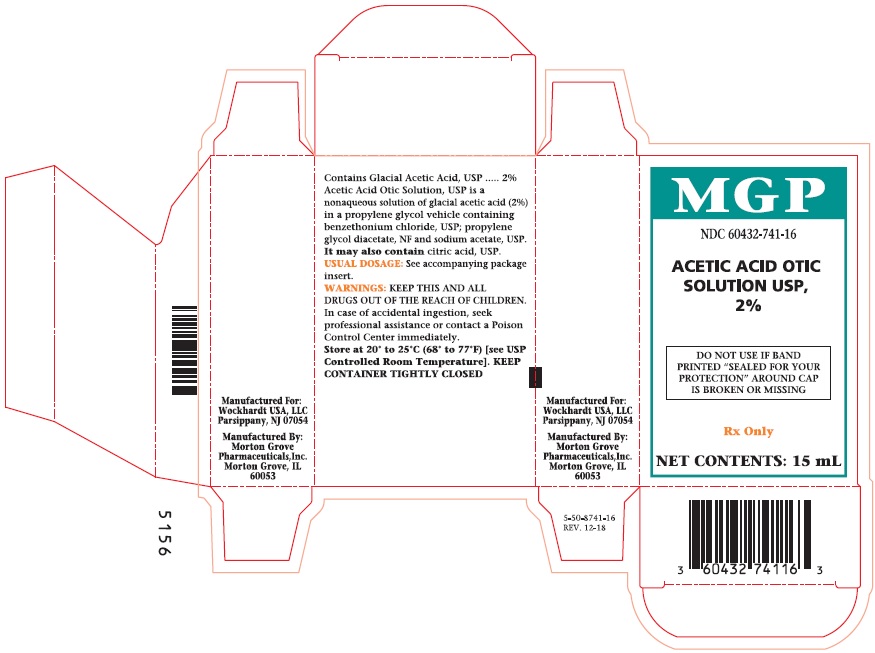 DRUG LABEL: ACETIC ACID
NDC: 60432-741 | Form: SOLUTION
Manufacturer: Morton Grove Pharmaceuticals, Inc.
Category: prescription | Type: HUMAN PRESCRIPTION DRUG LABEL
Date: 20190104

ACTIVE INGREDIENTS: ACETIC ACID 20 mg/1 mL
INACTIVE INGREDIENTS: PROPYLENE GLYCOL; PROPYLENE GLYCOL DIACETATE; BENZETHONIUM CHLORIDE; SODIUM ACETATE; ANHYDROUS CITRIC ACID

ACETIC ACID OTIC SOLUTION USP, 2%

DESCRIPTION

Acetic Acid Otic Solution, USP is a nonaqueous solution of glacial acetic acid, USP (2%), in a propylene glycol vehicle containing benzethonium chloride, USP (0.02%); propylene glycol diacetate, NF (3%) and sodium acetate, USP (0.015%). It may also contain citric acid, USP.

The molecular formula for acetic acid is CH3COOH, with a molecular weight of 60.05. The structural formula is:

Acetic Acid Otic Solution is available as a nonaqueous otic solution buffered at pH 3 for use in the external ear canal.

CLINICAL PHARMACOLOGY

Acetic acid is anti-bacterial and anti-fungal; propylene glycol is hydrophilic and provides a low surface tension; benzethonium chloride is a surface active agent that promotes contact of the solution with tissues.

INDICATIONS AND USAGE

For the treatment of superficial infections of the external auditory canal caused by organisms susceptible to the action of the antimicrobial.

CONTRAINDICATIONS

Hypersensitivity to Acetic Acid Otic Solution or any of the ingredients. Perforated tympanic membrane is considered a contraindication to the use of any medication in the external ear canal.

WARNINGS

Discontinue promptly if sensitization or irritation occurs.

PRECAUTIONS

Transient stinging or burning may be noted occasionally when the solution is first instilled into the acutely inflamed ear.

Pediatric Use

Safety and Effectiveness in pediatric patients below the age of 3 years have not been established.

ADVERSE REACTIONS

Stinging or burning may be noted occasionally; local irritation has occurred very rarely.

DOSAGE AND ADMINISTRATION

Carefully remove all cerumen and debris to allow Acetic Acid Otic Solution to contact infected surfaces directly. To promote continuous contact, insert a wick of cotton saturated with the solution into the ear canal; the wick may also be saturated after insertion. Instruct the patient to keep the wick in for at least 24 hours and to keep it moist by adding 3 to 5 drops of the solution every 4 to 6 hours. The wick may be removed after 24 hours but the patient should continue to instill 5 drops of Acetic Acid Otic Solution 3 or 4 times daily thereafter, for as long as indicated. In pediatric patients, 3 to 4 drops may be sufficient due to the smaller capacity of the ear canal.

HOW SUPPLIED

Acetic Acid Otic Solution USP, 2% is supplied in 15 mL measured drop, safety-tip plastic bottles.

RECOMMENDED STORAGE

Store at 20° to 25°C (68° to 77°F) [see USP Controlled Room Temperature].

KEEP CONTAINER TIGHTLY CLOSED

Rx Only

Product No.: 8741

Manufactured For:

Wockhardt USA, LLC

Parsippany, NJ 07054

Manufactured By:

Morton Grove Pharmaceuticals, Inc

Morton Grove, IL 60053

A50-8741-15

REV. 09-12

PRINCIPAL DISPLAY PANEL

MGP

NDC 60432-741-15

ACETIC ACID

OTIC

SOLUTION

USP, 2%

DO NOT USE IF BAND

PRINTED "SEALED FOR YOUR

PROTECTION" AROUND CAP

IS BROKEN OR MISSING.

Rx Only

NET CONTENTS:

15 mL

MGP

NDC 60432-741-16

ACETIC ACID

OTIC

SOLUTION

USP, 2%

DO NOT USE IF BAND

PRINTED "SEALED FOR YOUR

PROTECTION" AROUND CAP

IS BROKEN OR MISSING.

Rx Only

NET CONTENTS:

15 mL

Acetic Acid Carton